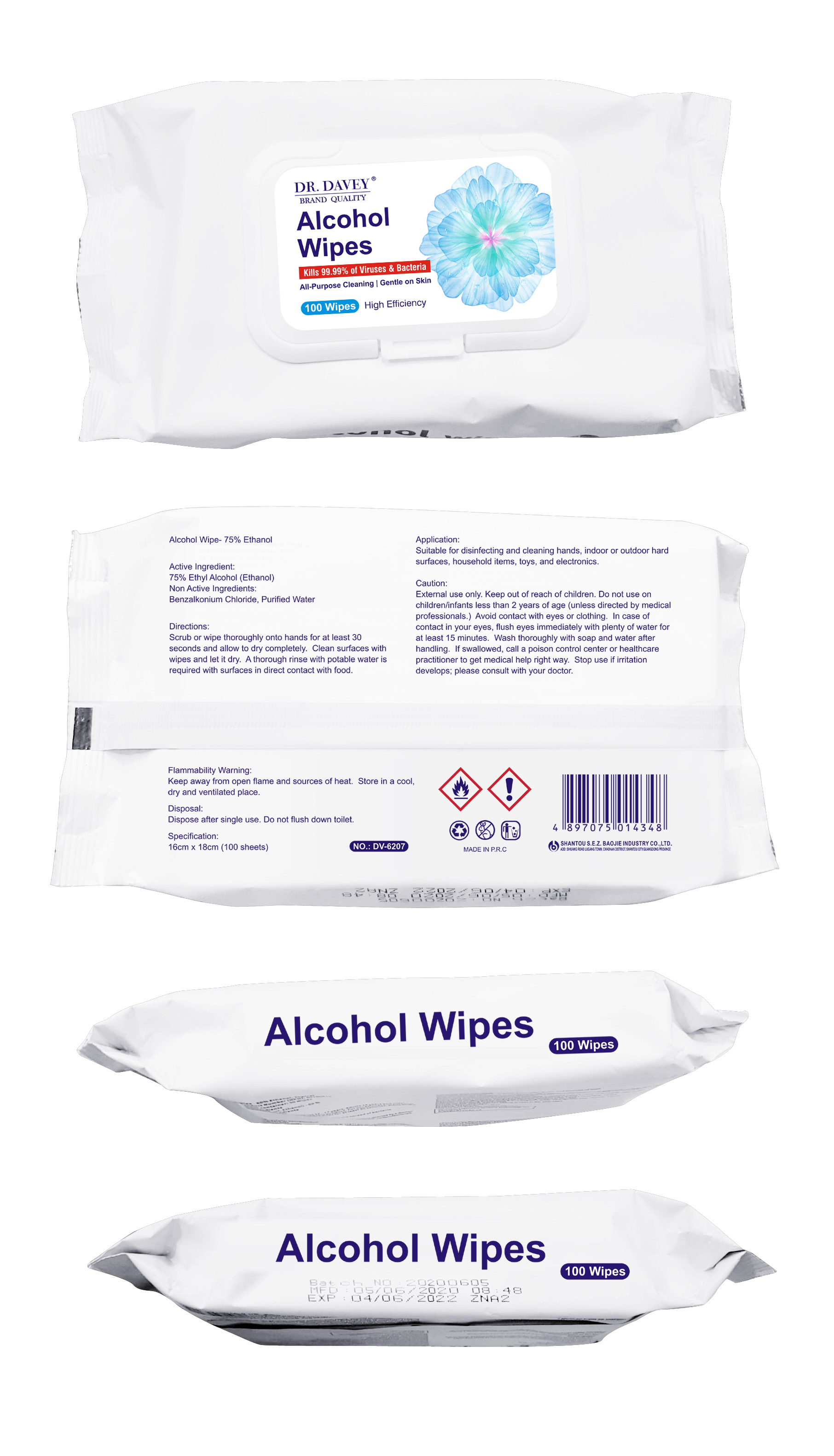 DRUG LABEL: Dr.Davey 75% alcohol wipes
NDC: 74913-900 | Form: CLOTH
Manufacturer: SHANTOU S.E.Z BAOJIE INDUSTRY CO., LTD
Category: otc | Type: HUMAN OTC DRUG LABEL
Date: 20200617

ACTIVE INGREDIENTS: ALCOHOL 75 mL/100 U
INACTIVE INGREDIENTS: BENZALKONIUM CHLORIDE 0.03 mL/100 U; WATER 24.97 mL/100 U

Dr.Davey 75% alcohol wipes